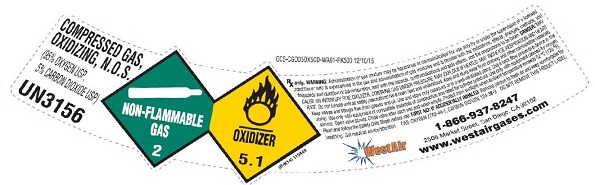 DRUG LABEL: Carbogen
NDC: 53440-008 | Form: GAS
Manufacturer: Westair Gases & Equipment, Inc.
Category: prescription | Type: HUMAN PRESCRIPTION DRUG LABEL
Date: 20251126

ACTIVE INGREDIENTS: OXYGEN 950 mL/1 L
INACTIVE INGREDIENTS: CARBON DIOXIDE 5 mL/1 L

carbon dixoide/oxygen mix

PACKAGE LABEL

COMPRESSED GAS, OXIDIZING, N.O.S. (95% OXYGEN USP, 5% CARBON DIOXIDE USP) UN3156 NON-FLAMMABLE GAS 2 OXIDIZER 5.1
Rx only. WARNING: Administration of gas mixture may be hazardous or contraindicated. For use only by or under the supervision of a licensed practitioner who is experienced in the use and administration of gas mixtures and is familiar with the indications, effects, dosages, methods, and frequency and duration of administration, and with the hazards, contraindications and side effects, and the precautions to be taken. DANGER: MAY CAUSE OR INTENSIFY FIRE; OXIDIZER CONTAINS GAS UNDER PESSURE; MAY EXPLODE IF HEATED. MAY INCREASE RESPIRATION AND HEART RATE. Do not handle until all safety precautions have been read and understood. Keep and store away from clothing and other combustible materials. Keep valves and fittings free from grease and oil. Use and store only outdoors or in a well-ventilated place. Use a back flow preventive device in the piping. Use only with equipment of compatible materials of construction and rated for cylinder pressure. Use only with equipment cleaned for oxygen service. Open valve slowly. Close valve after each use and when empty. Protect from sunlight when ambient temperature exceeds 52 degrees C (125 degrees F). Read and follow the Safety Data Sheet (SDS) before use. FIRST AID: IF ACCIDENTALLY INHALED: Remove person to fresh air and keep comfortable for breathing. Get medical advice/attention. CAS: OXYGEN 7782-44-7, CARBON DIOXIDE 124-28-9 DO NOT REMOVE THIS LABEL.
WestAir 1-866-937-8247 2506 Market Street, San Diego, CA 92102 www.westairgases.com